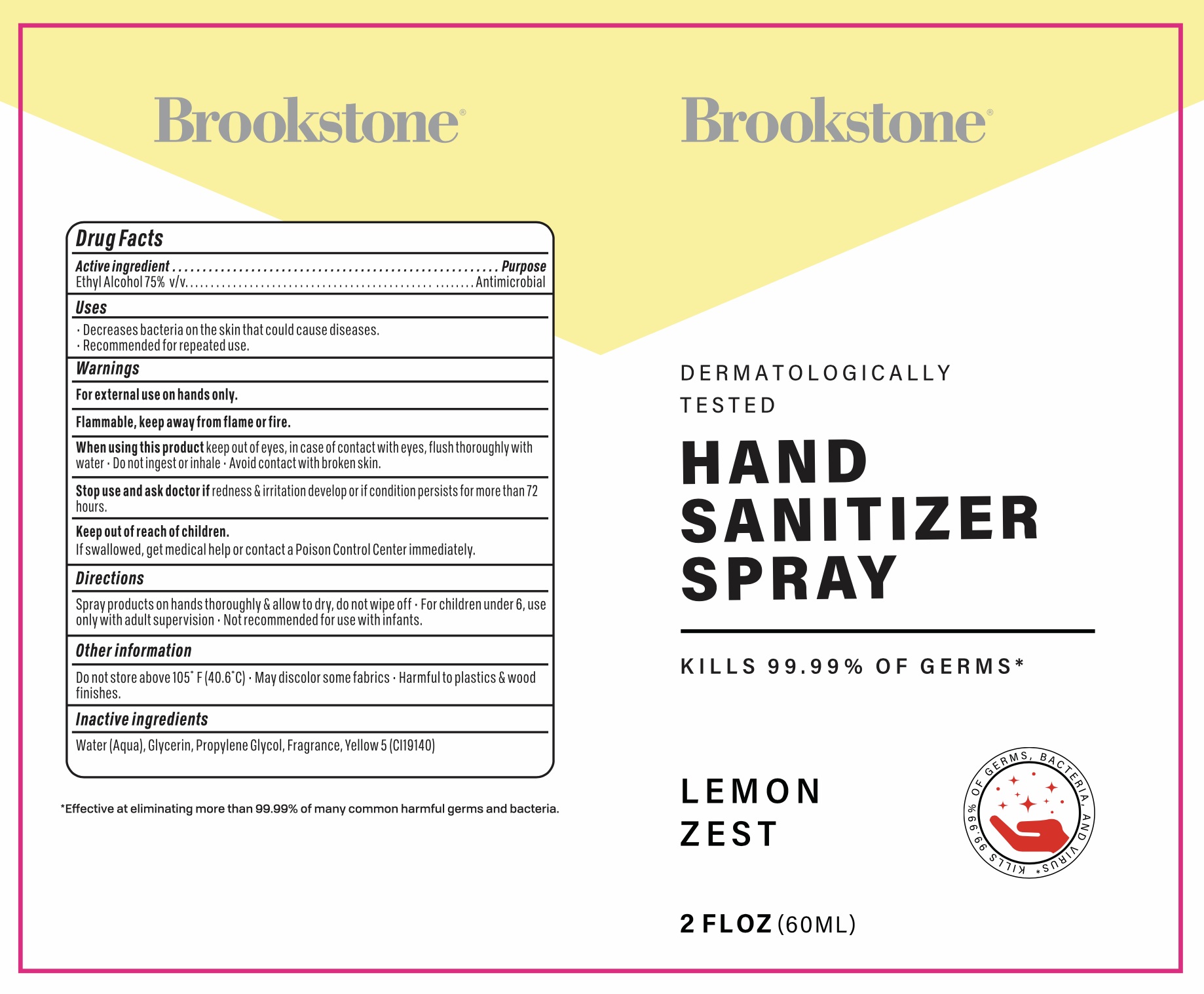 DRUG LABEL: Brookstone Lemon Zest Hand Sanitizer
NDC: 77731-084 | Form: SPRAY
Manufacturer: Argento sc by sicura inc.
Category: otc | Type: HUMAN OTC DRUG LABEL
Date: 20200917

ACTIVE INGREDIENTS: ALCOHOL 75 mL/100 mL
INACTIVE INGREDIENTS: GLYCERIN; WATER; PROPYLENE GLYCOL; FD&C YELLOW NO. 5

77731-084/AB0056LZ-2-Yel

Active Ingredient(s)

Ethyl Alcohol 75% v/v

Purpose:

Antimicrobial

Use

Decrease bacteria on skin that could cause diseases

Recommended for repeated use

Warnings

For external use only. Flammable, keep way from flame or fire

When using this product, keep out of eyes. In case of contact with eyes, flush thoroughly with water

Do not ingest or inhale

Avoid contact with broken skin

Stop use and ask a doctor

if irrigation and redness develop or if condition persists for more than 72 hours

Keep out of reach of children

if swallowed, get medical help or contact a Poison Control Center immediately

Directions

- Spray product on hands thoroughly and allow to dry, do not wipe off
- For children under 6, use under adult supervision
- Not recommended for use with infants

Other information

Do not store above 105F (40.6C)

May discolor some fabrics

Harmful to plastics and wood finishes

Inactive ingredients

Water, Glycerin, Propylene Glycol, Fragrance, Yellow 5 (CI19140)